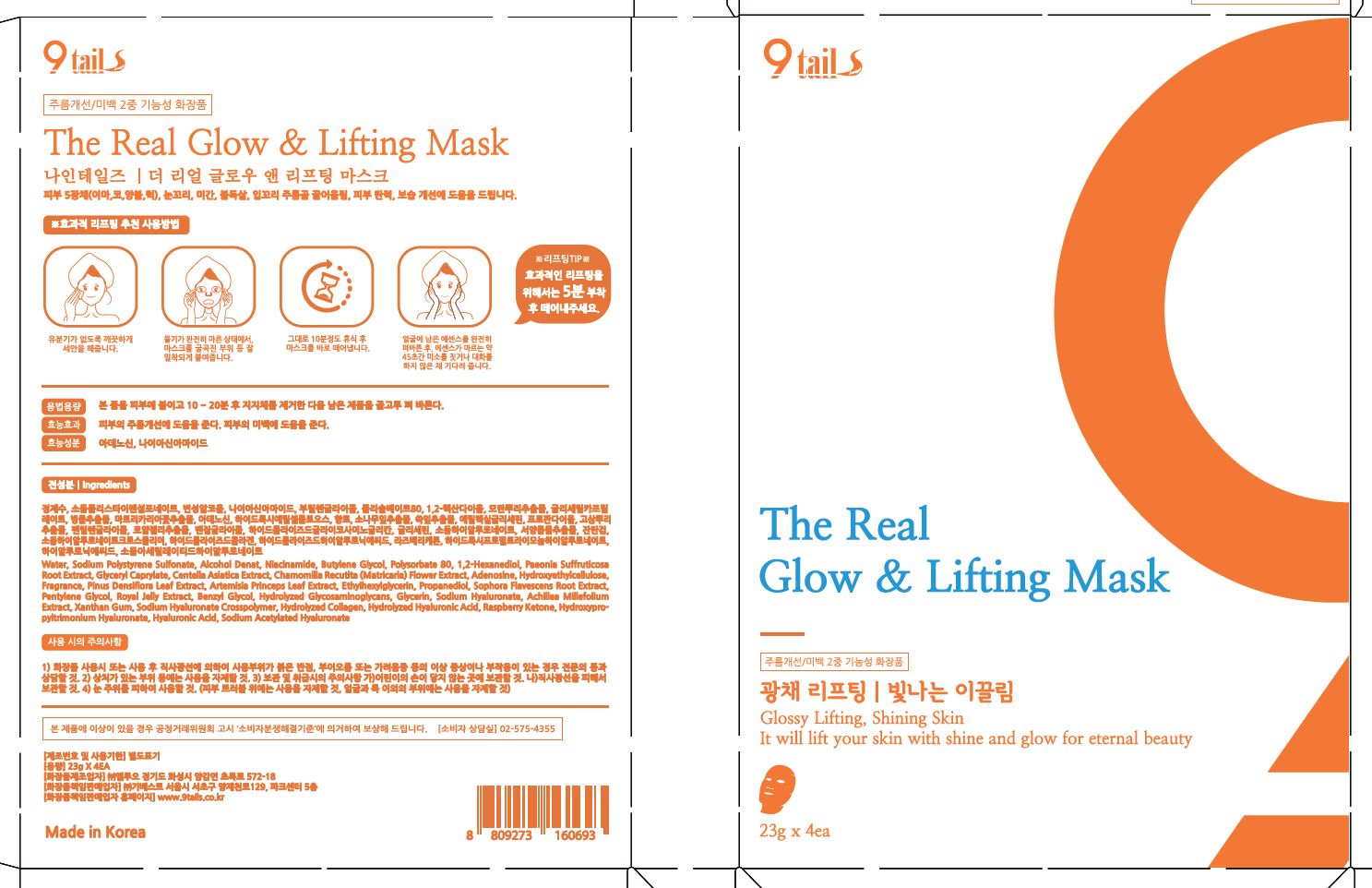 DRUG LABEL: The Real Glow Lifting Mask
NDC: 72176-0300 | Form: LIQUID
Manufacturer: GIBEST
Category: otc | Type: HUMAN OTC DRUG LABEL
Date: 20210522

ACTIVE INGREDIENTS: NIACINAMIDE 2 g/100 g; ADENOSINE 0.04 g/100 g
INACTIVE INGREDIENTS: WATER; GLYCERIN

ACTIVE INGREDIENT

adenosine, niacinamide

INACTIVE INGREDIENT

Water
Sodium Polystyrene Sulfonate
Alcohol Denat.
Niacinamide
Butylene Glycol
Polysorbate 80
1,2-Hexanediol
Paeonia Suffruticosa Root Extract
Glyceryl Caprylate
Centella Asiatica Extract
Chamomilla Recutita (Matricaria) Flower Extract
Adenosine
Hydroxyethylcellulose
Fragrance
Pinus Densiflora Leaf Extract
Artemisia Princeps Leaf Extract
Ethylhexylglycerin
Propanediol
Sophora Flavescens Root Extract
Pentylene Glycol
Royal Jelly Extract
Benzyl Glycol
Hydrolyzed Glycosaminoglycans
Glycerin
Sodium Hyaluronate
Achillea Millefolium Extract
Xanthan Gum
Sodium Hyaluronate Crosspolymer
Hydrolyzed Collagen
Hydrolyzed Hyaluronic Acid
Raspberry Ketone
Hydroxypropyltrimonium Hyaluronate
Hyaluronic Acid
Sodium Acetylated Hyaluronate

PURPOSE

wrinkle care, whitening

keep out or reach of the children

INDICATIONS AND USAGE

apply to the skin and leave 10 ~ 20 minutes, and remove the mask and spread the remaining solution evenly

WARNINGS

[Caution]

1. Use only directed.
2. Avoid stroing in extremely high or low temperatures and areas exposed to direct sunlight.
3. If irritation occurs, discontinue use.

DOSAGE AND ADMINISTRATION

for external use only